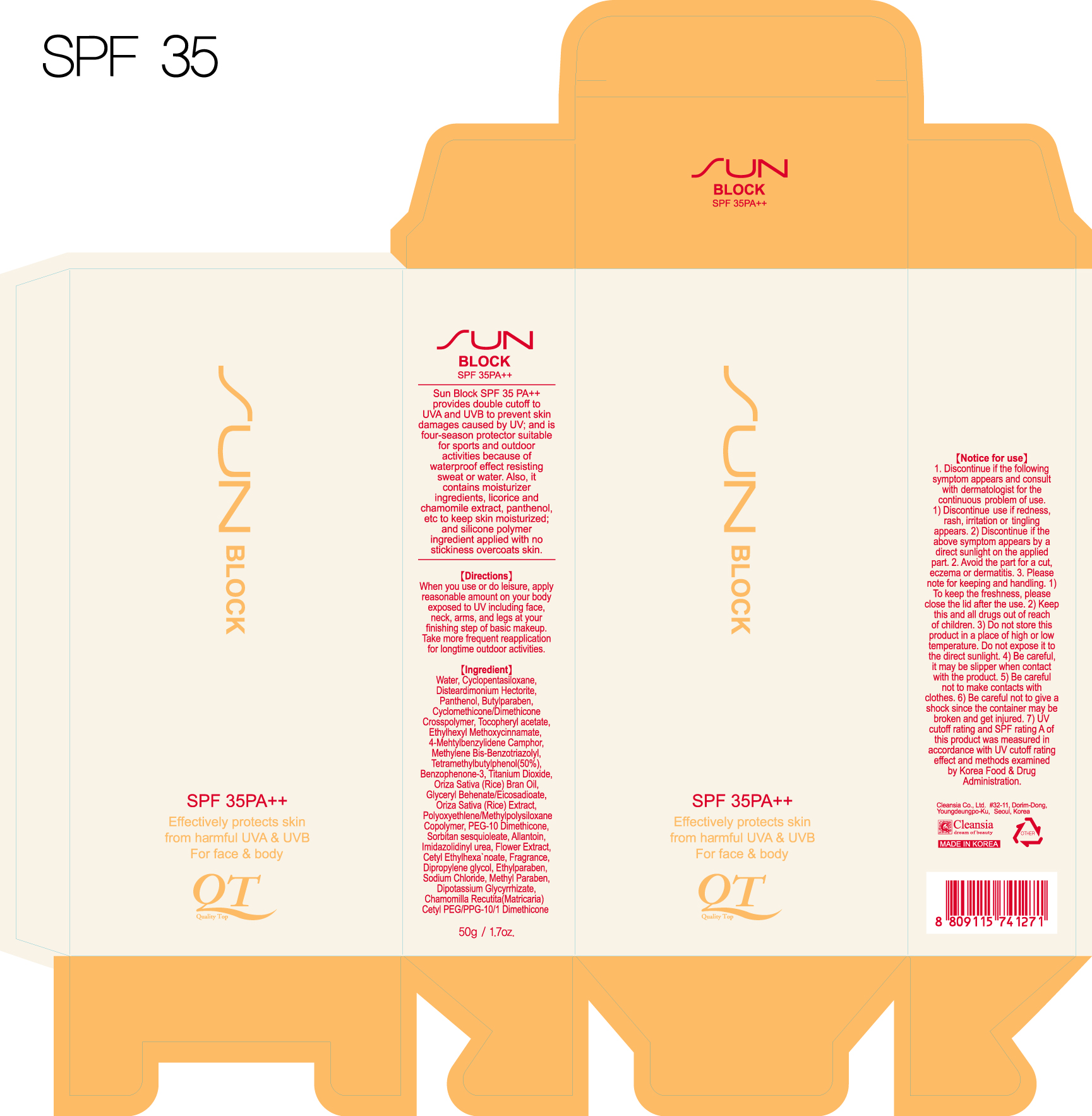 DRUG LABEL: QT SUN BLOCK
NDC: 45167-516 | Form: CREAM
Manufacturer: Cleansia Co Ltd
Category: otc | Type: HUMAN OTC DRUG LABEL
Date: 20100121

ACTIVE INGREDIENTS: OCTINOXATE 7.5 g/100 g; TITANIUM DIOXIDE 2.2 g/100 g; ENZACAMENE 2.0 g/100 g

Active Ingredients:
Ethylhexyl Methoxycinnamate, Titanium Dioxide, 4-Methylbenzylidene Camphor, Methylene Bis-Benzotriazolyl Tetramethylbutylphenol, Benzophenone-3

Inactive Ingredients:
Water, Cyclopentasiloxane, Disteardimonium Hectorite, Dimethiconol, Tocopheryl Acetate, PEG-10 Dimethicone, Cetyl PEG/PPG-10/1 Dimethicone, Sorbitan Sesquioleate, Glyceryl Behenate/Eicosadioate, Cetyl Ethylhexanoate, Cyclohexasiloxane, Propylene Glycol, Dipropylene Glycol, Allantoin, Aluminum Hydroxide, Stearic Acid, Xanthan Gum, Methylparaben, Sodium Chloride, Butylparaben, Imidazolidinyl Urea, Fragrance, Ethylparaben, Oryza Sativa (Rice) bran Oil, Oryza Sativa (Rice) Bran Extract

Directions:
When you use or do leisure, apply reasonable amount on your body exposed to UV including face, neck, arms and legs at your finishing step of basic makeup. Take more frequent reapplication for long time outdoor activities

Notice for Use:
1. Discontinue if the following symptom appears and consult with dermatologist for the continuous problem of use
a) Discontinue use if redness, rash, irritation or tingling appears
b) Discontinue if the above symptom appears by a direct sunlight on the applied part
2. Avoid the part for a cut, eczema or dermatitis

KEEP OUT OF REACH OF CHILDREN

Keep this and all drugs out of reach of children

PRECAUTIONS

Caution:
- Be careful it may be slippery when contact with the product
- Be careful not to make contact with clothes
- Be careful not to give a shock since the container may be broken and get injured

Storage and Handling:
- To keep the freshness, please close the lid after the use
- Do not store this product in a place of high or low temperature
- Do not expose it to the direct sunlight